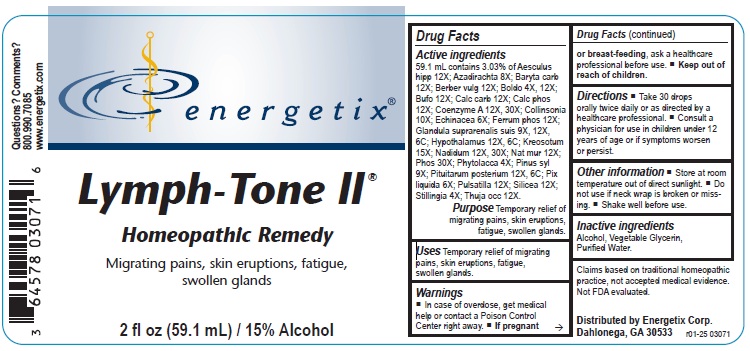 DRUG LABEL: Lymph-Tone II
NDC: 64578-0153 | Form: LIQUID
Manufacturer: Energetix Corporation
Category: homeopathic | Type: HUMAN OTC DRUG LABEL
Date: 20250715

ACTIVE INGREDIENTS: HORSE CHESTNUT 12 [hp_X]/59.1 mL; AZADIRACHTA INDICA BARK 8 [hp_X]/59.1 mL; BARIUM CARBONATE 12 [hp_X]/59.1 mL; BERBERIS VULGARIS ROOT BARK 12 [hp_X]/59.1 mL; PEUMUS BOLDUS LEAF 4 [hp_X]/59.1 mL; BUFO BUFO CUTANEOUS GLAND 12 [hp_X]/59.1 mL; OYSTER SHELL CALCIUM CARBONATE, CRUDE 12 [hp_X]/59.1 mL; TRIBASIC CALCIUM PHOSPHATE 12 [hp_X]/59.1 mL; COENZYME A 12 [hp_X]/59.1 mL; COLLINSONIA CANADENSIS ROOT 10 [hp_X]/59.1 mL; ECHINACEA ANGUSTIFOLIA 6 [hp_X]/59.1 mL; FERRUM PHOSPHORICUM 12 [hp_X]/59.1 mL; SUS SCROFA ADRENAL GLAND 9 [hp_X]/59.1 mL; BOS TAURUS HYPOTHALAMUS 12 [hp_X]/59.1 mL; WOOD CREOSOTE 15 [hp_X]/59.1 mL; NADIDE 12 [hp_X]/59.1 mL; SODIUM CHLORIDE 12 [hp_X]/59.1 mL; PHOSPHORUS 30 [hp_X]/59.1 mL; PHYTOLACCA AMERICANA ROOT 4 [hp_X]/59.1 mL; PINUS SYLVESTRIS LEAFY TWIG 9 [hp_X]/59.1 mL; BOS TAURUS PITUITARY GLAND 12 [hp_X]/59.1 mL; PINE TAR 6 [hp_X]/59.1 mL; PULSATILLA VULGARIS 12 [hp_X]/59.1 mL; SILICON DIOXIDE 12 [hp_X]/59.1 mL; STILLINGIA SYLVATICA ROOT 4 [hp_X]/59.1 mL; THUJA OCCIDENTALIS LEAFY TWIG 12 [hp_X]/59.1 mL
INACTIVE INGREDIENTS: WATER; ALCOHOL; GLYCERIN

Lymph-Tone II

Active ingredients(per drop)

Aesculus hipp 12X; Azadirachta 8X; Baryta carb 12X; Berber vulg 12X; Boldo 4X, 12X; Bufo 12X; Calc carb 12X; Calc phos 12X; Coenzyme A 12X, 30X; Collinsonia 10X; Echinacea 6X; Ferrum phos 12X; Glandula suprarenalis suis 9X, 12X, 6C; Hypothalamus 12X, 6C; Kreosotum 15X; Nadidum 12X, 30X; Nat mur 12X; Phos 30X; Phytolacca 4X; Pinus syl 9X; Pituitarum posterium 12X, 6C; Pix liquida 6X; Pulsatilla 12X; Silicea 12X; Stillingia 4X; Thuja occ 12X.

Purpose

Temporary relief of migrating pains, skin eruptions, fatigue, swollen glands.

Uses

Temporary relief of migrating pains, skin eruptions, fatigue, swollen glands.

Warnings

- In case of overdose, get medical help or contact a Poison Control Center right away.
- If pregnant or breast feeding, ask a healthcare professional before use.

- Keep out of reach of children.

Directions

- Take 30 drops orally twice daily or as directed by a healthcare professional.
- Consult a physician for use in children under 12 years of age or if symptoms worsen or persist.

Other information

- Store at room temperature out of direct sunlight.
- Do not use if neck wrap is broken or missing.
- Shake well before use.

Inactive ingredients

Alcohol, Vegetable Glycerin, Purified Water.

QUESTIONS

Distributed by

Energetix Corp.

Dahlonega, GA 30533

Questions? Comments?

800.990.7085

www.energetix.com

PACKAGE LABEL

energetix®

Lymph-Tone II

Homeopathic Remedy

Migrating pains, skin eruptions, fatigue, swollen glands.

2 fl oz (59.1 mL) / 15% Alcohol

Purpose

Temporary relief of migrating pains, skin eruptions, fatigue, swollen glands.